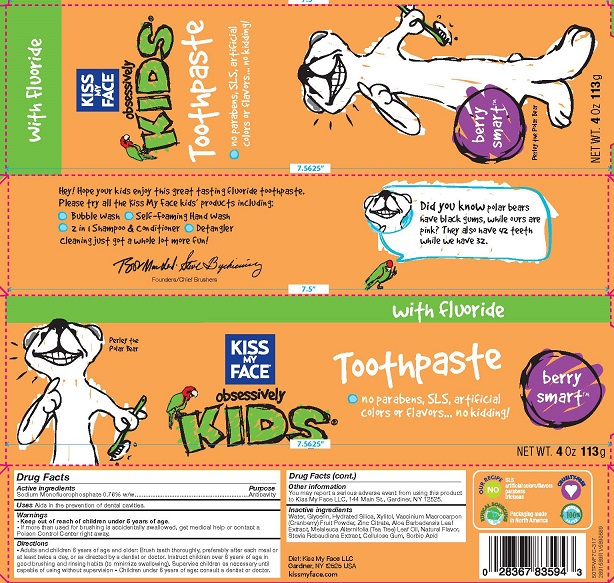 DRUG LABEL: Kiss My Face
NDC: 65364-404 | Form: PASTE, DENTIFRICE
Manufacturer: Kiss My Face, LLC
Category: otc | Type: HUMAN OTC DRUG LABEL
Date: 20190220

ACTIVE INGREDIENTS: SODIUM MONOFLUOROPHOSPHATE 0.76 g/100 g
INACTIVE INGREDIENTS: ZINC CITRATE; SORBIC ACID; WATER; TEA TREE OIL; CARBOXYMETHYLCELLULOSE SODIUM, UNSPECIFIED FORM; STEVIA REBAUDIUNA LEAF; VACCINIUM MACROCARPON WHOLE; ALOE VERA LEAF; GLYCERIN; HYDRATED SILICA; XYLITOL

Kiss My Face Kids Toothpaste Berry Smart

Drug Facts

Active ingredient

Sodium Monofluorphosphate 0.76% w/w

Purpose

Anticavity

Uses

Aids in the prevention of dental cavities

Warnings

- Keep out of reach of children under 6 years of age.
- If more than used for brushing is accidentally swallowed, get medical help or contact a Poison Control Center right away.

Directions

- Adults and children 6 years of age and older: Brush teeth thoroughly, preferably after each meal or at least twice a day, or as directed by a dentist or doctor. Instruct children over 6 years of age in good brushing and rinsing habits (to minimize swallowing). Supervise children as necessary until capable of using without supervision.
- Children under 6 years of age: consult a dentist or doctor

Other information

You may report a serious adverse event from using this product to Kiss My Face, LLC, 144 Main Street, Gardiner, NY 12525.

INACTIVE INGREDIENT

Inactive ingredients: Water, Glycerin, Hydrated Silica, Xylitol, Vaccinium Macrocarpon (Cranberry) Fruit Powder, Zinc Citrate, Aloe Barbadensis Leaf Extract, Melaleuca Alternifolia (Tea Tree) Leaf Oil, Natural Flavor, Stevia Rebaudiana Extract, Cellulose Gum, Sorbic Acid

Dist. Kiss My Face LLC, Gardiner, NY 12525 USA

PACKAGE LABEL

KISS MY FACE®

obsessively kids®

Toothpaste with fluoride

berry smart™

no parabens, SLS, artificial colors or flavors...no kidding!

NET WT. 4 OZ (113 g)